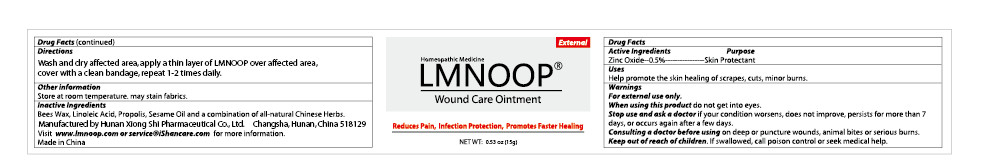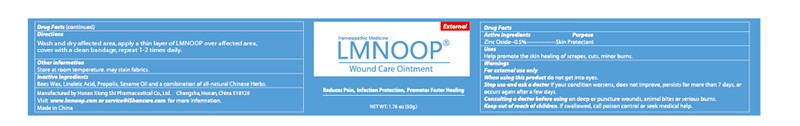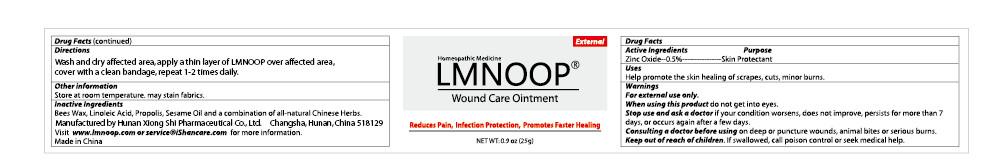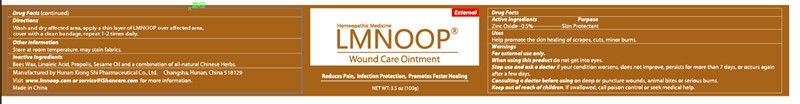 DRUG LABEL: LMNOOP Wound Care
NDC: 73252-139 | Form: OINTMENT
Manufacturer: Hunan Xiong Shi Pharmaceutical Co., Ltd
Category: homeopathic | Type: HUMAN OTC DRUG LABEL
Date: 20241019

ACTIVE INGREDIENTS: CALENDULA OFFICINALIS FLOWER 2 g/100 g
INACTIVE INGREDIENTS: PROPOLIS WAX; SESAME OIL; YELLOW WAX; GANODERMA LUCIDUM WHOLE; EUCALYPTUS RADIATA LEAF OIL; ANGELICA SINENSIS ROOT; LAVENDER OIL; MORUS ALBA BARK; SOPHORA FLAVESCENS ROOT

Active Ingredients

Zinc Oxide--0.5%

Inactive Ingredients

Bees Wax, Linoleic Acid, Propolis, Sesame Oil and a combination of all-natural Chinese Herbs

Keep out of reach of children.

If swallowed, call poison control or seek medical help.

Consulting a doctor before using

on deep or puncture wounds, animal bites or serious burns.

Stop use and ask a doctor

if your condition worsens, does not improve, persists for more than 7 days, or occurs again after a few days.

Purpose

Skin Protectant

Other information

Store at room temperature. may stain fabrics

Directions

Wash with mild skin cleanser. Pat dry or allow to air dry. Apply an ample amount of ointment over affected skin. Cover with a clean bandage. Repeat procedure every 12 hours until skin improves or as directed by a doctor.

When using this product

Do not get into eyes

Warnings

For external use only,

When using this product do not get into eyes